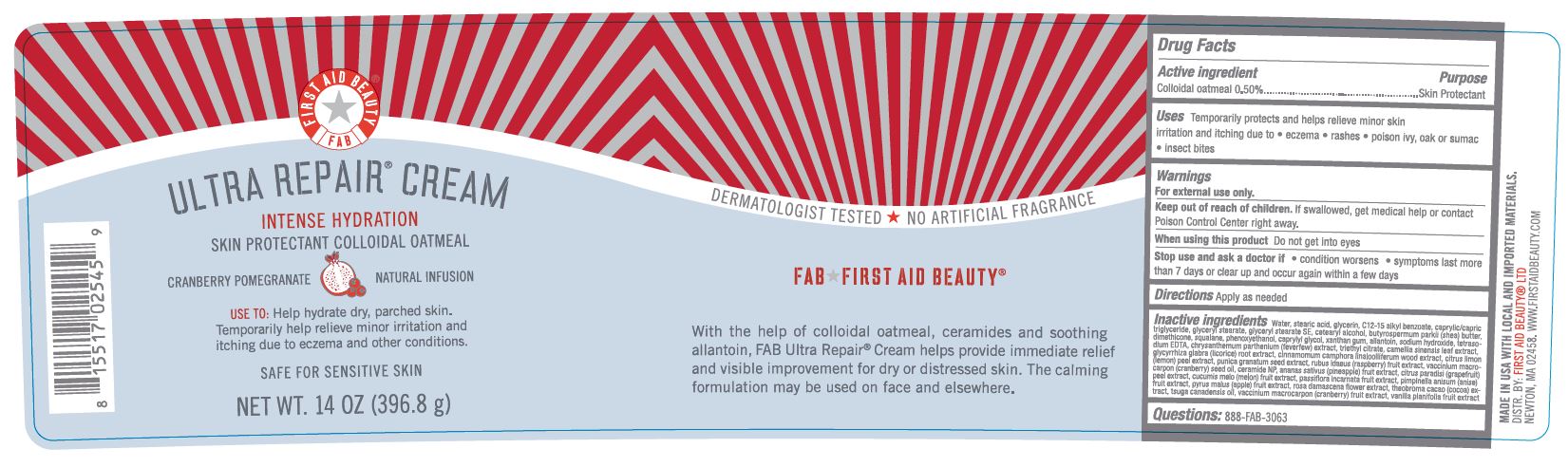 DRUG LABEL: First Aid Beauty FAB Ultra Repair Intense Hydration Skin Protectant Cranberry Pomegranate
NDC: 69423-565 | Form: CREAM
Manufacturer: The Procter & Gamble Manufacturing Company
Category: otc | Type: HUMAN OTC DRUG LABEL
Date: 20251218

ACTIVE INGREDIENTS: OATMEAL 0.5 g/100 g
INACTIVE INGREDIENTS: MUSKMELON; PASSIFLORA INCARNATA FRUIT; MENTHA PIPERITA LEAF; APPLE; CRANBERRY SEED OIL; TANACETUM PARTHENIUM WHOLE; CETOSTEARYL ALCOHOL; SQUALANE; DIMETHICONE; EDETATE SODIUM; GLYCERYL STEARATE SE; ALKYL (C12-15) BENZOATE; GREEN TEA LEAF; CAPRYLYL GLYCOL; SODIUM HYDROXIDE; PHENOXYETHANOL; SHEA BUTTER; GLYCYRRHIZA GLABRA; WATER; GLYCERIN; ALLANTOIN; GLYCERYL MONOSTEARATE; MEDIUM-CHAIN TRIGLYCERIDES; STEARIC ACID; XANTHAN GUM; PINEAPPLE; CERAMIDE NP; VANILLA BEAN; RASPBERRY; LEMON PEEL; TRIETHYL CITRATE; CRANBERRY; POMEGRANATE SEED; GRAPEFRUIT PEEL; ANISE; ROSA DAMASCENA FLOWER; COCOA; TSUGA CANADENSIS LEAF OIL

First Aid Beauty FAB Ultra Repair Cream Skin Protectant Cranberry Pomegranate

Drug Facts

Active ingredients

Colloidal Oatmeal 0.5%

Purpose

Skin Protectant

Uses

- Temporarily protects and helps relieve minor skin irritation and itching due to eczema, rashes, poison ivy, oak or sumac, insect bites

Warnings

For external use only.

Keep out of reach of children. If swallowed, get medical help or contact a Poison Control Center right away.

WHEN USING

Do not get into eyes.

Stop use and ask a doctor if condition worsens, symptoms last more than 7 days or clear up and occur again within a few days

Directions

Apply as needed

INACTIVE INGREDIENT

Water, stearic acid, glycerin, c12-15 alkyl benzoate, caprylic/capric triglyceride, glyceryl stearate, glyceryl stearate SE, cetearyl alcohol, butyrospermum parkii (shea) butter, dimethicone, squalene, phenoxyethanol, caprylyl glycol. xanthan gum, allantoin, sodium hydroxide, tetrasodium EDTA, chrysanthemum parthenium (feverfew) extract, triethyl citrate, camellia sinensis leaf extract, glycyrrhiza glabra (licorice) root extract, cinnamomum camphora linalooliferum wood extract, citrus limon (lemon) peel extract, punica granatum seed extract, rubus idaeus (raspberry) fruit extract, vaccinium macrocarpon (cranberry) seed oil, ceramide NP, ananas sativus (pineapple) fruit extract, citrus paradisi (grapefruit) peel extract, cucumis melo (melon) fruit extract, passiflora incarnata fruit extract, pimpinella anisum (anise) fruit extract, pyrus malus (apple) fruit extract, rosa damascene flower extract, Theobroma cacao (cocoa) extract, tsuga canadensis oil, vaccinium macrocarpon (cranberry) fruit extract, vanilla planifolia fruit extract

Questions:

888-FAB-3063

MADE IN USA

FIRST AID BEAUTY LTD

NEWTON, MA 02458

WWW.FIRSTAIDBEAUTY.COM

PRINCIPAL DISPLAY PANEL - 14.0 oz (396.8 g)

First Aid Beauty

FAB

Ultra Repair® Cream

Intense Hydration

Skin Protectant Colloidal Oatmeal

Cranberry Pomegranate Natural Infusion

Net Wt. 14.0 oz (396.8 g)